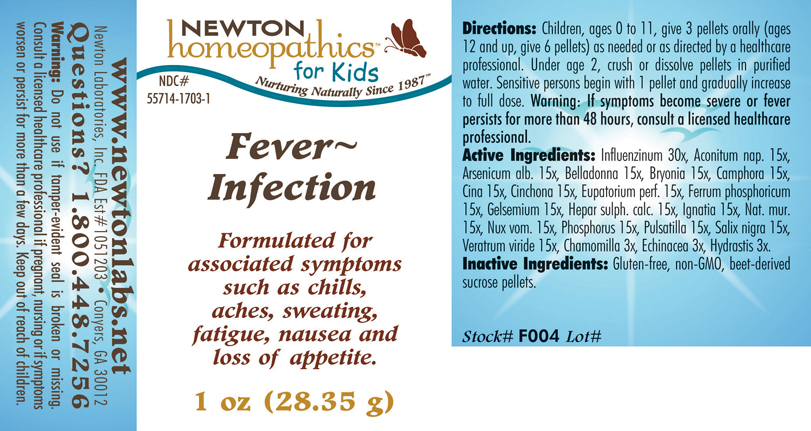 DRUG LABEL: Fever Infection 
NDC: 55714-1703 | Form: PELLET
Manufacturer: Newton Laboratories, Inc.
Category: homeopathic | Type: HUMAN OTC DRUG LABEL
Date: 20110301

ACTIVE INGREDIENTS: Influenza A Virus 30 [hp_X]/1 g; Aconitum Napellus 15 [hp_X]/1 g; Arsenic Trioxide 15 [hp_X]/1 g; Atropa Belladonna 15 [hp_X]/1 g; Bryonia Alba Root 15 [hp_X]/1 g; Camphor (natural) 15 [hp_X]/1 g; Artemisia Cina Pre-flowering Top 15 [hp_X]/1 g; Cinchona Officinalis Bark 15 [hp_X]/1 g; Eupatorium Perfoliatum Flowering Top 15 [hp_X]/1 g; Gelsemium Sempervirens Root 15 [hp_X]/1 g; Calcium Sulfide 15 [hp_X]/1 g; Strychnos Ignatii Seed 15 [hp_X]/1 g; Sodium Chloride 15 [hp_X]/1 g; Strychnos Nux-vomica Seed 15 [hp_X]/1 g; Phosphorus 15 [hp_X]/1 g; Pulsatilla Vulgaris 15 [hp_X]/1 g; Salix Nigra Bark 15 [hp_X]/1 g; Veratrum Viride Root 15 [hp_X]/1 g; Matricaria Recutita 3 [hp_X]/1 g; Echinacea, Unspecified 3 [hp_X]/1 g; Goldenseal 3 [hp_X]/1 g; Ferrosoferric Phosphate 15 [hp_X]/1 g; Influenza B Virus 30 [hp_X]/1 g
INACTIVE INGREDIENTS: Sucrose

Fever - Infection

INDICATIONS & USAGE SECTION

Fever - Infection Formulated for associated symptoms such as chills, aches, sweating, fatigue, nausea and loss of appetite.

DOSAGE & ADMINISTRATION SECTION

Directions: Children, ages 0 to 11, give 3 pellets orally (ages 12 and up, give 6 pellets) as needed or as directed by a healthcare professional. Under age 2, crush or dissolve pellets in purified water. Sensitive persons begin with 1 pellet and gradually increase to full dose. Warning: If symptoms become severe or fever persists for more than 48 hours, consult a licensed health care professional.

OTC - ACTIVE INGREDIENT SECTION

Influenzinum 30x, Aconitum nap. 15x, Arsenicum alb. 15x, Belladonna 15x, Bryonia 15x, Camphora 15x, Cina 15x, Cinchona 15x, Eupatorium perf. 15x, Ferrum phosphoricum 15x, Gelsemium 15x, Hepar sulph. calc. 15x, Ignatia 15x, Nat. mur.15x, Nux vom. 15x, Phosphorus 15x, Pulsatilla 15x, Salix nigra 15x, Veratrum viride 15x, Chamomilla 3x, Echinacea 3x, Hydrastis 3x.

OTC - PURPOSE SECTION

Formulated for associated symptoms such as chills, aches, sweating, fatigue, nausea and loss of appetite.

INACTIVE INGREDIENT SECTION

Inactive Ingredients: Gluten-free, non-GMO, beet-derived sucrose pellets.

QUESTIONS SECTION

www.newtonlabs.net Newton Laboratories, Inc. FDA Est # 1051203 - Conyers, GA 30012
Questions? 1.800.448.7256

WARNINGS SECTION

Warning: Do not use if tamper - evident seal is broken or missing. Consult a licensed healthcare professional if p. regnant, nursing or if symptoms worsen or persist for more than a few days. Keep out of reach of children.

OTC - PREGNANCY OR BREAST FEEDING SECTION

Consult a licensed healthcare professional if pregnant, nursing or if symptoms worsen or persist for more than a few days.

OTC - KEEP OUT OF REACH OF CHILDREN SECTION

Keep out of reach of children.